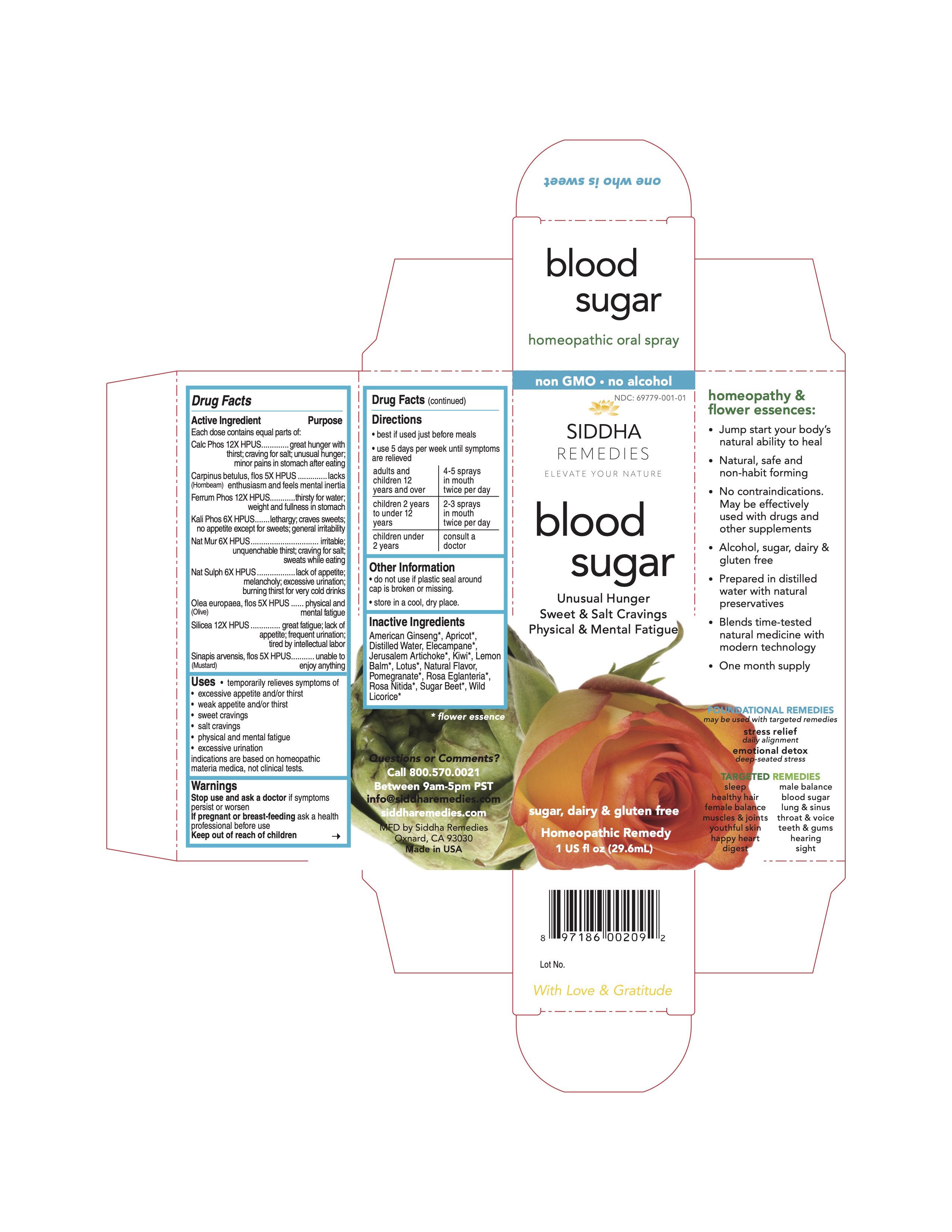 DRUG LABEL: blood sugar
NDC: 69779-001 | Form: SPRAY
Manufacturer: Siddha Flower Essences, LLC
Category: homeopathic | Type: HUMAN OTC DRUG LABEL
Date: 20251231

ACTIVE INGREDIENTS: TRIBASIC CALCIUM PHOSPHATE 12 [hp_X]/29.6 mL; CARPINUS BETULUS FLOWER 12 [hp_X]/29.6 mL; FERROSOFERRIC PHOSPHATE 12 [hp_X]/29.6 mL; POTASSIUM PHOSPHATE, DIBASIC 6 [hp_X]/29.6 mL; SODIUM CHLORIDE 6 [hp_X]/29.6 mL; SODIUM SULFATE 6 [hp_X]/29.6 mL; OLEA EUROPAEA FLOWER 5 [hp_X]/29.6 mL; SILICON DIOXIDE 12 [hp_X]/29.6 mL; SINAPIS ARVENSIS FLOWERING/FRUITING TOP 5 [hp_X]/29.6 mL
INACTIVE INGREDIENTS: AMERICAN GINSENG; APRICOT; JERUSALEM ARTICHOKE; MELISSA OFFICINALIS FLOWERING TOP; NELUMBO NUCIFERA FLOWER; PUNICA GRANATUM FLOWER; WATER; BETA VULGARIS; GLYCYRRHIZA GLABRA

Drug Facts

Active Ingredient

Each dose contains equal parts of:
Cal Phos 12X HPUS
Carpinus betulus, flos (Hornbeam) 5X HPUS
Ferrum Phos 12X HPUS
Kali Phos 6X HPUS
Nat Mur 6X HPUS
Nat Sulph 6X HPUS
Olea europaea, flos (Olive) 5X HPUS
Silicea 12X HPUS
Sinapis arvensis, flos (Mustard) 5X HPUS

Purpose

Each dose contains equal parts of:
Cal Phos 12X HPUS.........................................great hunger with thirst; craving for salt; unusual hunger; minor pains in stomach after eating
Carpinus betulus, flos (Hornbeam) 5X HPUS.......lacks enthusiasm and feels mental inertia
Ferrum Phos 12X HPUS...................................thirsty for water; weight and fullness in stomach
Kali Phos 6X HPUS..........................................lethargy; craves sweets; not appetite except for sweets; general irritability
Nat Mur 6X HPUS............................................irritable; unquenchable thirst; craving for salt; sweats while eating
Nat Sulph 6X HPUS.........................................lacks appetite; melancholy; excessive urination; burning thirst for very cold drinks
Olea europaea, flos (Olive) 5X HPUS..................physical and mental fatigue
Silicea 12X HPUS............................................great fatigue; lack or appetite; frequent urination; tired by intellectual labor
Sinapis arvensis, flos (Mustard) 5X HPUS..........unable to enjoy anything

Uses

- temporarily relieves symptoms of
- excessive appetite and/or thirst
- weak appetite and/or thirst
- sweet cravings
- salt cravings
- physical and mental fatigue
- excessive urination

indications are based on homeopathic materia medica, not clinical tests.

Warnings

Stop use and ask a doctor

if symptoms persist or worsen

PREGNANCY OR BREAST FEEDING

If pregnant or breast-feeding ask a health professional before use

Keep out of reach of children

Directions

- best if used just before meals
- use 5 days per week until symptoms are relieved

adults and children 12 years and over | 4-5 sprays in mouth twice per day
children 2 years to under 12 years | 2-3 sprays in mouth twice per day
children under 2 years | consult a doctor

Other Information

- do not use if plastic seal around cap is broken or missing.
- store in a cool, dry place.

Inactive Ingredients

American Ginseng*, Apricot*, Elecampane*, Jerusalem Artichoke*, Kiwi*, Lemon Balm*, Lotus*, Natural Flavor, Pomegranate*, Purified Water, Rosa Eglanteria*, Rosa Nitida*, Sugar Beet*, Wild Licorice*

*flower essence

Questions or Comments?

Call 800.570.0021

Between 9am-5pm PST

info@siddhaflowers.com

siddhaflowers.com

MFD by Siddha Flower Essences
Oxnard, CA 93030

Made in USA

Side Panel

homeopathy and flower essences:

- Jump start your body's natural ability to heal
- Natural, safe and non-habit forming
- No contraindications. May be effectively used with drugs and other supplements
- Alcohol, sugar, dairy and gluten free
- Prepared in purified water with natural preservatives
- Blends time-tested natural medicine with modern technology
- One month supply

FOUNDATIONAL REMEDIES
may be used with targeted remedies

stress relief
daily alignment
emotional detox
deep-seated stress

TARGETED REMEDIES

sleep male balance

healthy hair blood sugar

female balance lung and sinus

muscles and joints throat and voice

youthful skin teeth and gums

happy heart hearing

digest sight

Principal Display Panel

non GMO - no alcohol

blood sugar

Unusual Hunger
Sweet and Salt Cravings
Physical and Mental Fatigue

sugar, dairy and gluten free

Homeopathic Remedy
1 US fl oz (29.6mL)